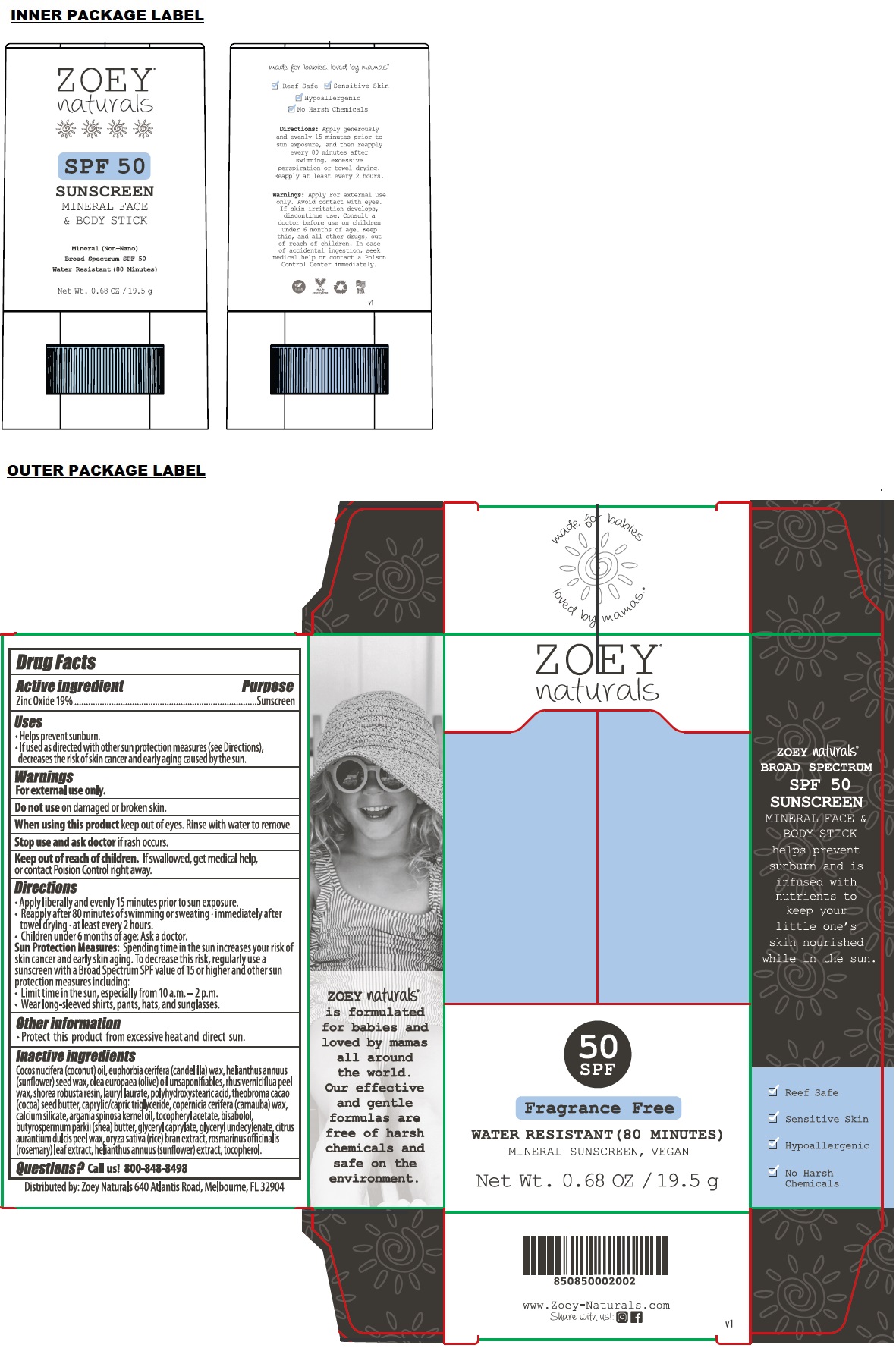 DRUG LABEL: Zoey naturals Broad Spectrum SPF 50 Fragrance Free Sunscreen
NDC: 70793-033 | Form: STICK
Manufacturer: Absolutely Natural
Category: otc | Type: HUMAN OTC DRUG LABEL
Date: 20241211

ACTIVE INGREDIENTS: ZINC OXIDE 19 g/100 g
INACTIVE INGREDIENTS: COCONUT OIL; CANDELILLA WAX; HELIANTHUS ANNUUS SEED WAX; OLEA EUROPAEA (OLIVE) OIL UNSAPONIFIABLES; TOXICODENDRON VERNICIFLUUM FRUIT RIND WAX; SHOREA ROBUSTA RESIN; LAURYL LAURATE; POLYHYDROXYSTEARIC ACID (2300 MW); COCOA BUTTER; MEDIUM-CHAIN TRIGLYCERIDES; CARNAUBA WAX; CALCIUM SILICATE; ARGAN OIL; .ALPHA.-TOCOPHEROL ACETATE; LEVOMENOL; SHEA BUTTER; GLYCERYL MONOCAPRYLATE; GLYCERYL 1-UNDECYLENATE; ORANGE PEEL WAX; RICE BRAN; ROSEMARY; HELIANTHUS ANNUUS FLOWERING TOP; TOCOPHEROL

ZOEY® naturals Broad Spectrum SPF 50 Fragrance Free MINERAL SUNSCREEN

Active ingredient

Zinc Oxide 19%

Purpose

Sunscreen

Uses

• Helps prevent sunburn.
• If used as directed with other sun protection measures (see Directions), decreases the risk of skin cancer and early aging caused by the sun.

Warnings

For external use only.

Do not use on damaged or broken skin.

When using this product keep out of eyes. Rinse with water to remove.

Stop use and ask doctor if rash occurs.

Keep out of reach of children. If swallowed, get medical help, or contact Poison Control right away.

Directions

• Apply liberally and evenly 15 minutes prior to sun exposure.
• Reapply after 80 minutes of swimming or sweating • immediately after towel drying • at least every 2 hours.
• Children under 6 months of age: Ask a doctor.
Sun Protection Measures: Spending time in the sun increases your risk of skin cancer and early skin aging. To decrease this risk, regularly use a sunscreen with a Broad Spectrum SPF value of 15 or higher and other sun protection measures including:
• Limit time in the sun, especially from 10 a.m. - 2 p.m.
• Wear long-sleeved shirts, pants, hats, and sunglasses.

Other information

• Protect this product from excessive heat and direct sun.

Inactive ingredients

Cocos nucifera (coconut) oil, euphorbia cerifera (candelilla) wax, helianthus annuus (sunflower) seed wax, olea europaea (olive) oil unsaponifiables, rhus verniciflua peel wax, shorea robusta resin, lauryl laurate, polyhydroxystearic acid, theobroma cacao (cocoa) seed butter, caprylic/capric triglyceride, copernicia cerifera (carnauba) wax, calcium silicate, argania spinosa kernel oil, tocopheryl acetate, bisabolol, butyrospermum parkii (shea) butter, glyceryl caprylate, glyceryl undecylenate, citrus aurantium dulcis peel wax, oryza sativa (rice) bran extract, rosmarinus officinalis (rosemary) leaf extract, helianthus annuus (sunflower) extract, tocopherol.

Questions?

Call us! 800-848-8498

WATER RESISTANT (80 MINUTES)

MINERAL SUNSCREEN, VEGAN

MINERAL FACE & BODY STICK helps prevent sunburn and is infused with nutrients to keep your little one's skin nourished while in the sun.

√ Reef Safe

√ Sensitive Skin

√ Hypoallergenic

√ No Harsh Chemicals

ZOEY naturals® is formulated for babies and loved by mamas all around the world. Our effective and gentle formulas are free of harsh chemicals and safe on the environment.

Distributed by: Zoey Naturals 640 Atlantis Road, Melbourne, FL 32904

www. Zoey-Naturals.com

made for babies. loved by mamas.®

Crueltyfree

MADE IN USA